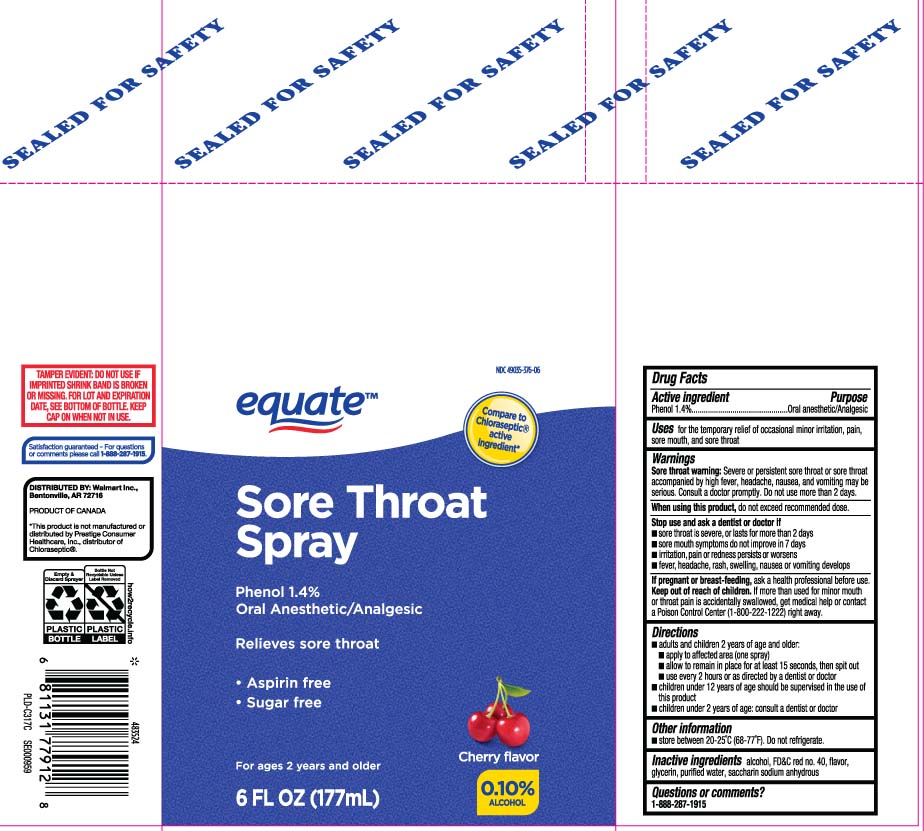 DRUG LABEL: Sore Throat
NDC: 49035-376 | Form: SPRAY
Manufacturer: EQUATE (Wal-Mart Stores, Inc.) (see also WAL-MART INC)
Category: otc | Type: HUMAN OTC DRUG LABEL
Date: 20251216

ACTIVE INGREDIENTS: PHENOL 1.4 g/100 mL
INACTIVE INGREDIENTS: ALCOHOL; FD&C RED NO. 40; GLYCERIN; WATER; SACCHARIN SODIUM

Drug Facts

Active ingredient

Phenol 1.4%

Purpose

Oral Anesthetic/Analgesic

Uses

for the temporary relief of occasional minor irritation, pain, sore mouth, and sore throat

Warnings

Sore throat warning: Severe or persistent sore throat or sore throat that accompanied by high fever, headache, nausea, and vomiting may be serious. Consult a doctor promptly. Do not use more than 2 days.

When using this product,

do not exceed recommended dose.

Stop use and ask a dentist or doctor if

- sore throat is severe, or lasts for more than 2 days
- sore mouth symptoms do not improve in 7 days
- irritation, pain or redness persists or worsens
- fever, headache, rash, swelling, nausea or vomiting develops

If pregnant or breast-feeding,

ask a health professional before use.

Keep out of reach of children.

If more than used for minor mouth or throat pain is accidentally swallowed, get medical help or contact a Poison Control Center (1-800-222-1222) right away.

Directions

- adults and children 2 years of age and older:
  - apply to affected area (one spray)
  - allow to remain in place for at least 15 seconds, then spit out
  - use every 2 hours as directed by a doctor or dentist
- children under 12 years of age should be supervised in the use of this product
- children under 6 years of age, consult a doctor or dentist

Other information

- store between 20º-25ºC (68º-77ºF). Do not refrigerate.

Inactive ingredients

alcohol, FD&C red #40, flavor, glycerin, purified water, saccharin sodium anhydrous

Questions or comments?

Call 1-888-287-1915

Principal Display Panel

Compare to Chloraseptic® active ingredient*

Sore Throat Spray

Phenol 1.4%

Oral Anesthetic / Analgesic Spray

Relieves sore throat

- Aspirin free
- Sugar Free

For ages 2 years and older

Cherry Flavor

0.10% ALCOHOL

FL OZ (mL)

*This product is not manufactured or distributed by Prestige Consumer healthcare, Inc., distributor of Chloraseptic®.

TAMPER EVIDENT: DO NOT USE IF IMPRINTED SHRINK BAND IS BROKEN OR MISSING. FOR LOT AND EXPIRATION DATE, SEE BOTTOM OF BOTTLE KEEP CAP ON WHEN NOT IN USE

Distributed by:

Walmart Inc.,

Bentonville, AR 72716

Package Label

EQUATE Sore Throat Spray Cherry Flavor